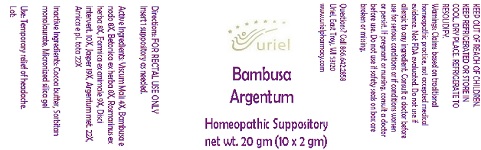 DRUG LABEL: Bambusa Argentum
NDC: 48951-2135 | Form: SUPPOSITORY
Manufacturer: Uriel Pharmacy Inc.
Category: homeopathic | Type: HUMAN OTC DRUG LABEL
Date: 20191119

ACTIVE INGREDIENTS: VISCUM ALBUM FRUITING TOP 4 [hp_X]/1 g; STACHYS OFFICINALIS 8 [hp_X]/1 g; ROSMARINUS OFFICINALIS FLOWERING TOP 8 [hp_X]/1 g; FORMICA RUFA 9 [hp_X]/1 g; BOS TAURUS INTERVERTEBRAL DISC 10 [hp_X]/1 g; SILICON DIOXIDE 19 [hp_X]/1 g; SILVER 22 [hp_X]/1 g; ARNICA MONTANA 22 [hp_X]/1 g; BAMBUSA VULGARIS WHOLE 8 [hp_X]/1 g
INACTIVE INGREDIENTS: SORBITAN MONOLAURATE; COCOA BUTTER

Bambusa Argentum

INDICATIONS AND USAGE

Directions: FOR RECTAL USE ONLY.

DOSAGE AND ADMINISTRATION

Insert 1 suppository as needed.

ACTIVE INGREDIENT

Active Ingredients: Viscum Mali 4X, Bambusa e nodo 8X, Betonica ex herba 8X, Rosmarinus ex herba 8X, Formica ex animale 9X, Disci intervert. 10X, Jasper 19X, Argentum met. 22X, Arnica e pl. tota 22X

INACTIVE INGREDIENT

Inactive Ingredients: Cocoa butter, Sorbitan monolaurate, Micronized silica gel

PURPOSE

Use: Temporary relief of headache.

KEEP OUT OF REACH OF CHILDREN.

WARNINGS

KEEP REFRIGERATED OR STORE IN
COOL, DRY PLACE. REFRIGERATE TO RESOLIDIFY.
Warnings: Claims based on traditional homeopathic practice, not accepted medical evidence. Not FDA evaluated. Do not use if allergic to any ingredient. Consult a doctor before use for serious conditions or if conditions worsen or persist. If pregnant or nursing, consult a doctor before use. Do not use if safety seals on box are broken or missing.

Questions? Call 866.642.2858
Uriel, East Troy, WI 53120
www.urielpharmacy.com